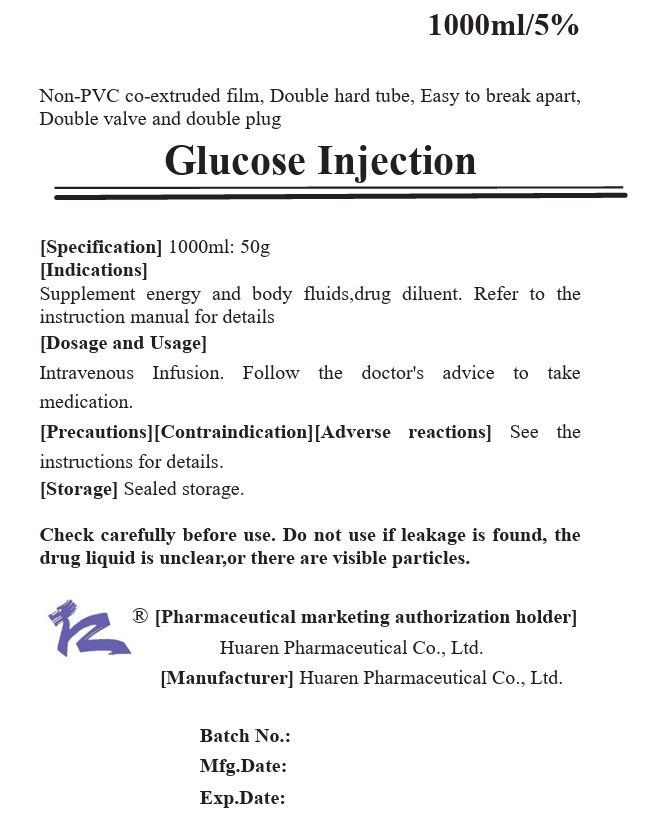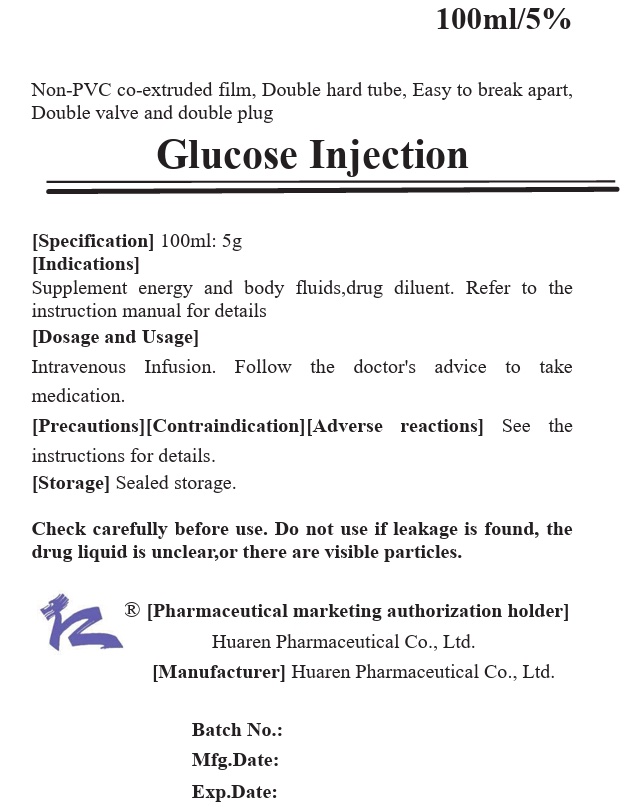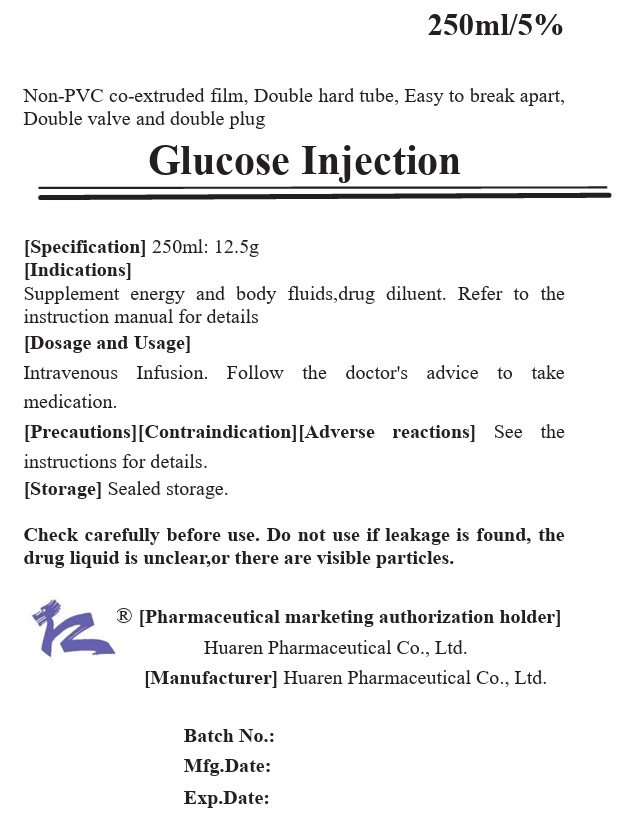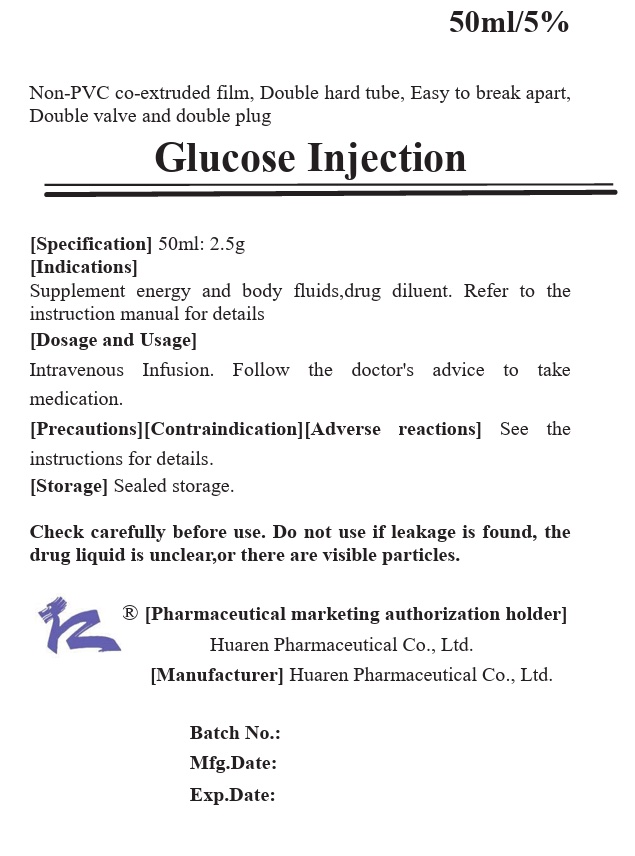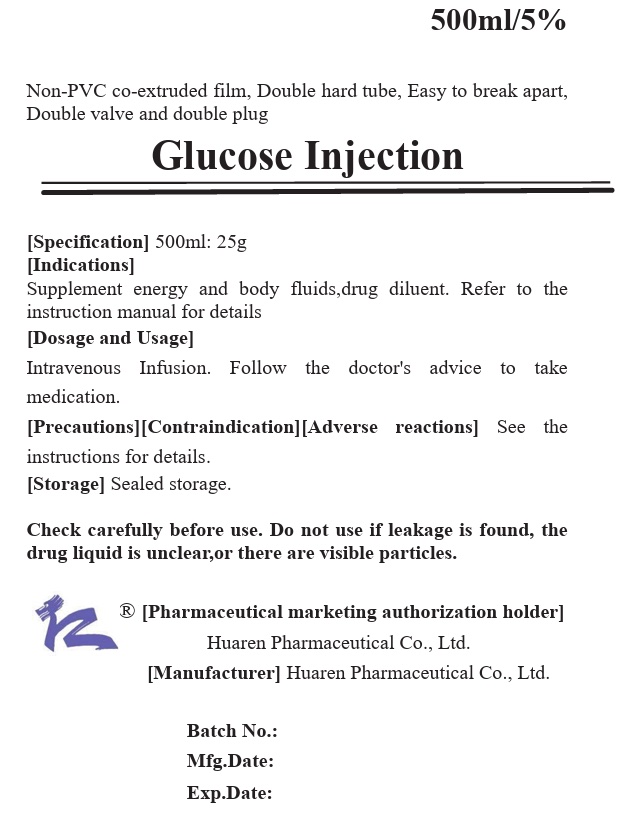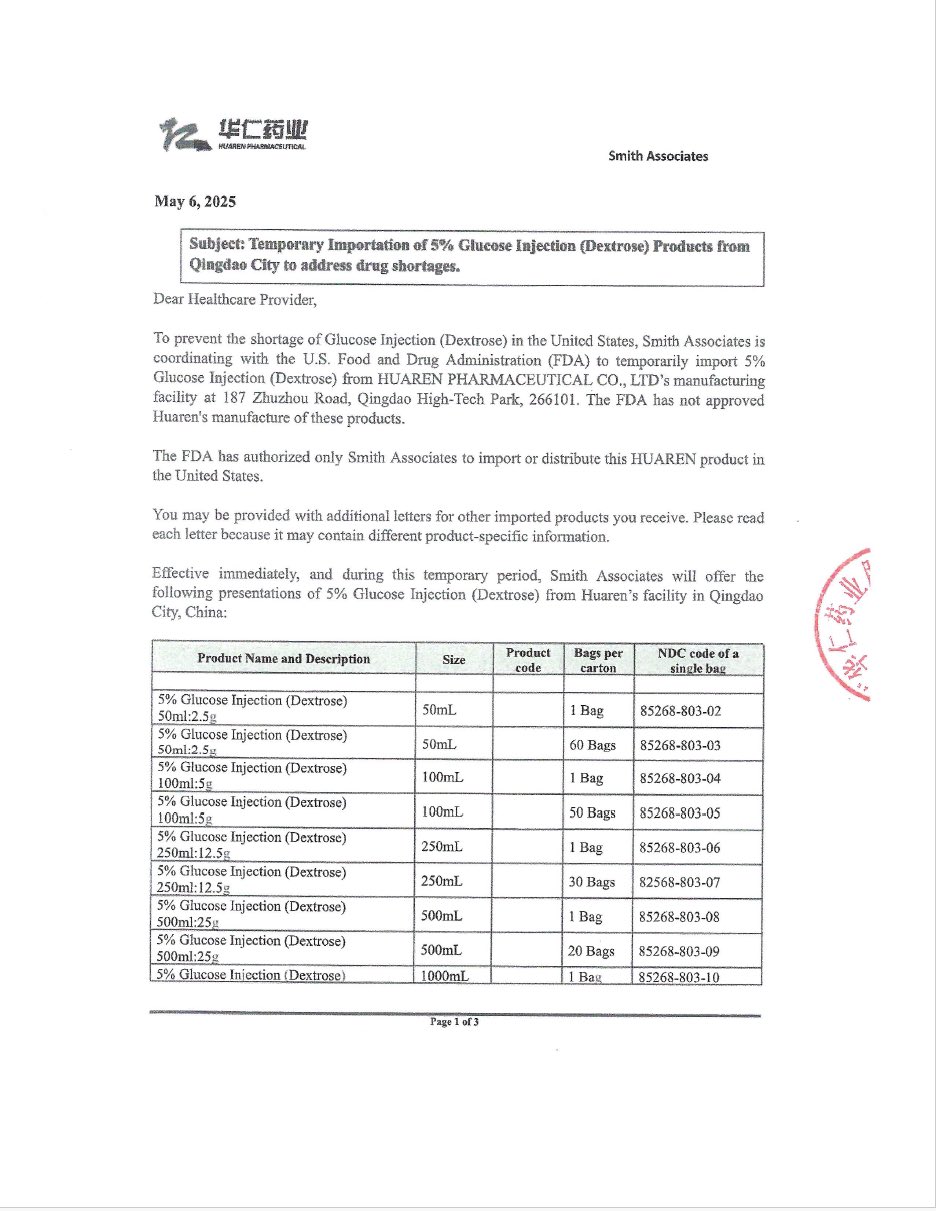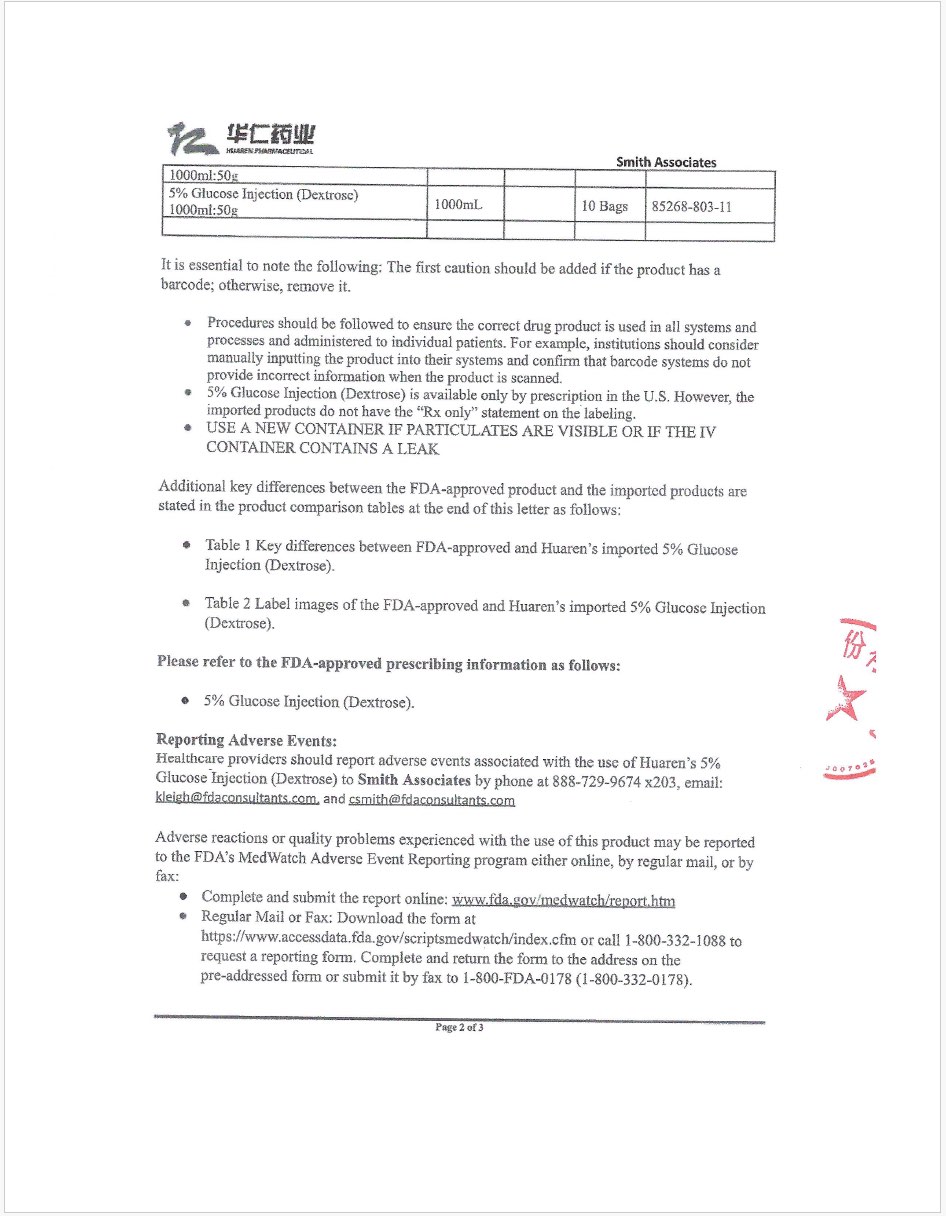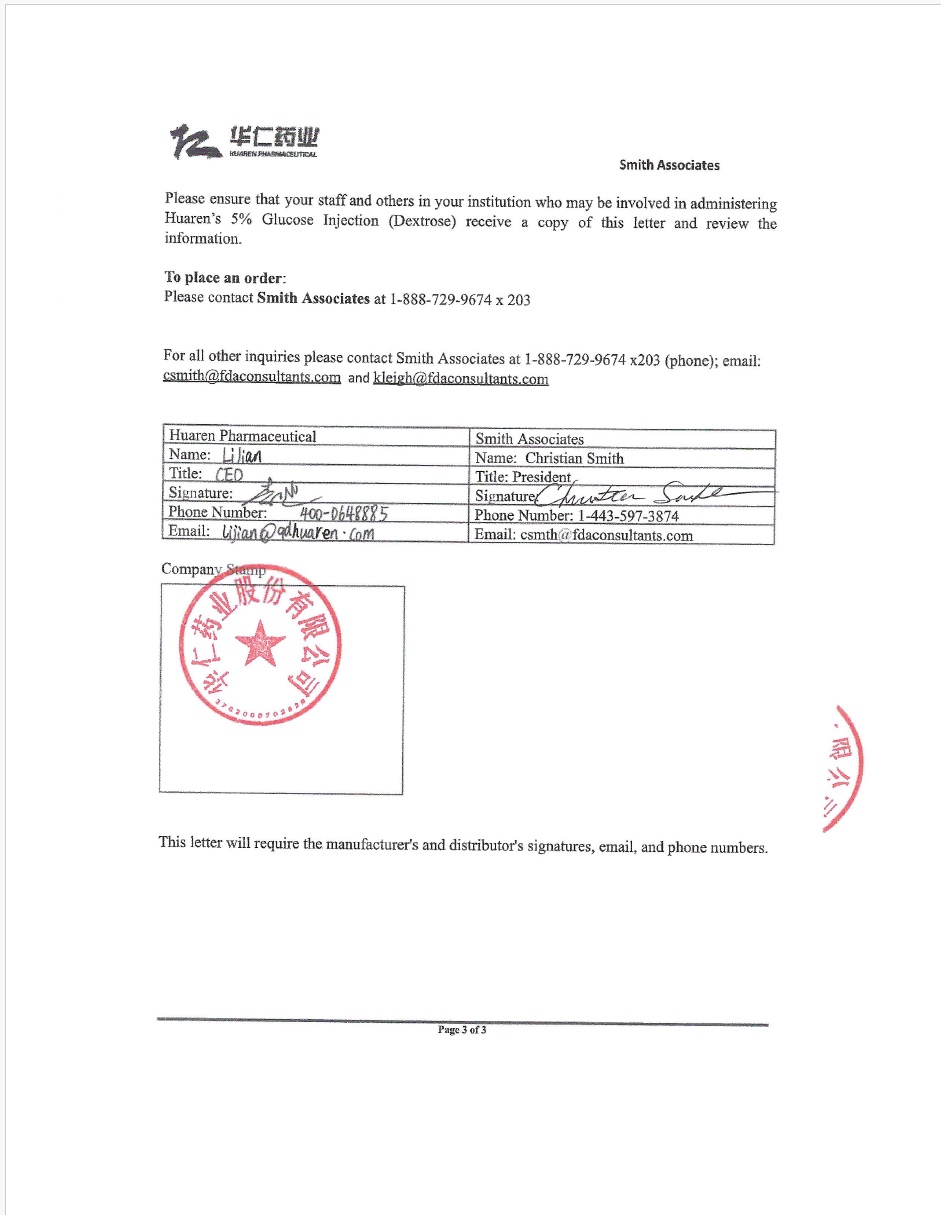 DRUG LABEL: Dextrose 5%
NDC: 85268-803 | Form: INJECTION, SOLUTION
Manufacturer: Huaren Pharmaceutical Co., Ltd.
Category: prescription | Type: HUMAN PRESCRIPTION DRUG LABEL
Date: 20250424

ACTIVE INGREDIENTS: ANHYDROUS DEXTROSE 5 g/100 mL
INACTIVE INGREDIENTS: WATER

Dextrose 5% - Q (EUA)

GLUCOSE (Dextrose) INJECTION, USP BAG

Instructions for Glucose (Dextrose) Injection

Please read the instructions carefully and use under the guidance of a physician.

Check carefully before use. Do not use if leakage is found, the drug liquid is unclear, or there are visible particles.

INGREDIENTS

This product is a sterilized aqueous solution of glucose.

General Name: Glucose injection

Molecular formula: C6H12O6·H2O

Molecular weight: 198.17

Auxiliary material name: Dilute hydrochloric acid

CHARACTER

This product is colorless or almost colorless clear liquid.

INDICATIONS

(1) Energy and fluid supplementation;It is used for underfeeding or massive fluid loss caused by various reasons (such as vomiting, diarrhea, etc.), total intravenous nutrition, and starvation ketosis.

(2) Drug diluents.

SPECIFICATION

（1）50ml:2.5g（2）50ml:5g（3）100ml：5g（4）100ml:10g（5）250ml:12.5g（6）250ml:25g（7）500ml:25g（8）500ml:50g（9）1000ml:50g（10）1000ml:100g

USAGE AND DOSAGE

Intravenous infusion. Medication as prescribed.

ADVERSE REACTIONS

1.Eating less, long-term simple supply of glucose solution can appear hypokalemia, hyponatremia and other electrolyte disorders. 2.Excessive infusion of this product may cause palpitations, arrhythmia, dyspnea, and even acute left heart failure in patients with cardiac insufficiency.

3.Hypophosphatemia is easy to occur when combined with insulin without paying attention to phosphate supplement.

4.Phlebitis may occur at the injection site.

【Taboos】

1. Uncontrolled diabetic ketoacidosis;

2. Hyperglycemic nonketotic hyperosmolar state.

PRECAUTIONS

1. Periodic paralysis, hypokalemia patients should be used with caution;

2. Stress or glucocorticoid induced hyperglycemia should be used with caution; Patients with edema, cardiac and renal insufficiency and liver cirrhosis ascites are prone to water retention, and the infusion volume should be controlled. Drip velocity should be controlled especially in patients with cardiac insufficiency.

3. Should be carefully checked before use, such as found leakage, solution turbidity, foreign bodies, etc., discarded.

4. Should be used in sterile conditions.

MEDICATION IN PREGNANT WOMEN AND LACTATING WOMEN

Too fast and too much fluid infusion may cause palpitation, arrhythmia and even acute left heart failure.

MEDICATION IN CHILDREN

Too fast and too much fluid infusion may cause palpitation, arrhythmia and even acute left heart failure.

MEDICATION IN THE ELDERLY

Too fast and too much fluid infusion may cause palpitation, arrhythmia and even acute left heart failure.

DRUG INTERACTIONS

The experiment was not performed and no reliable reference was available.

DRUG OVERDOSE

The experiment was not performed and no reliable reference was available.

PHARMACOLOGY AND TOXICOLOGY

Glucose is an important nutrient component of the human body. Every 1 gram of glucose can produce 4 kilocalories of heat energy, so it is used to supplement heat.

PHARMACOKINETICS

It can be converted into glycogen and fat for storage. The ability of a normal human body to utilize glucose is 6mg/kg per minute.

STORAGE

Sealed storage

VALIDITY

(1) The validity period of 250ml and 500ml products is 36 months.

(2) The validity period of 50ml, 100ml and 1000ml products is 24 months.

PACKAGE

1. Plastic infusion bag (non-PVC co-extrusion film, double hard pipe, easy to break apart, double valve and double plug). 50ml/ bag, 100ml/ bag, 250ml/ bag, 500ml/ bag, 1000ml/ bag. 2

. Plastic infusion bag (non-PVC co-extruded film, double hard tube, easy to break apart, double valve double plug, double layer sterile packaging). 50ml/ bag, 100ml/ bag, 250ml/ bag, 500ml/ bag, 1000ml/ bag.

OTHER INFORMATION

【Executive standard】

Pharmacopoeia of the People's Republic of China (2020, Volume II)

【Pharmaceutical marketing authorization holder】

Name: Huaren Pharmaceutical Co., Ltd. Registered Address: No. 187, Zhuzhou Road, Qingdao High-tech Park

【Manufacturer】Enterprise Name: Huaren Pharmaceutical Co., Ltd. Production Address: No. 187, Zhuzhou Road, Qingdao High-tech Park Zip code: 266101 Telephone number: 0532-67709071 0532-67709728 Fax number: 0532-88702625